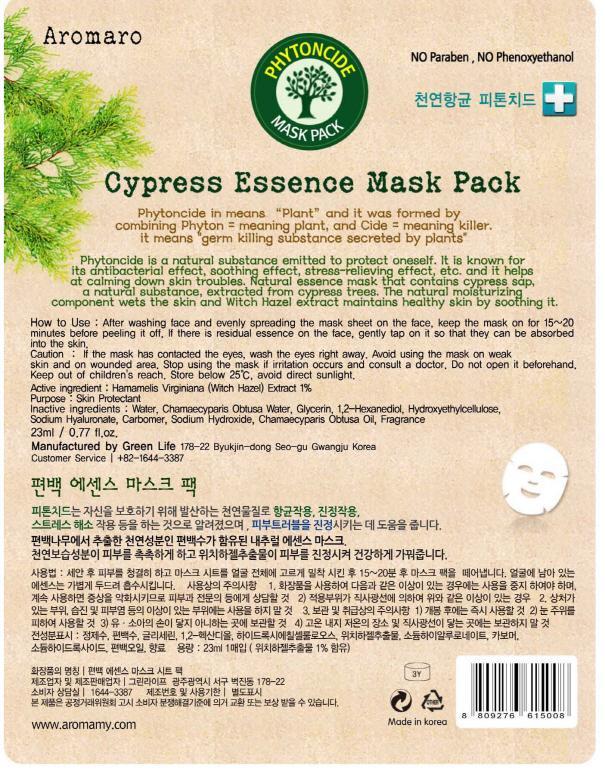 DRUG LABEL: CYPRESS ESSENCE MASK PACK
NDC: 52219-010 | Form: PATCH
Manufacturer: GREEN LIFE
Category: otc | Type: HUMAN OTC DRUG LABEL
Date: 20121009

ACTIVE INGREDIENTS: Witch Hazel 0.23 g/23 mL
INACTIVE INGREDIENTS: Water; Glycerin; 1,2-Hexanediol

ACTIVE INGREDIENT

Active ingredient: Hamamelis Virginiana (Witch Hazel) Extract 1%

INACTIVE INGREDIENT

Inactive ingredients:
Aqua Water, Chamaecyparis Obtusa Water, Glycerin, 1,2-Hexanediol, Hydroxyethylcellulose, Sodium Hyaluroate, Carbomer, Sodium Hydroxide, Chamaecyparis Obtusa Oil, Fragrance

PURPOSE

Purpose: Skin Protectant

WARNINGS

Caution:
If the mask has contacted the eyes, wash the eyes right away.
Avoid using the mask on weak skin and on wounded area.
Stop use if irritation occurs and consult a doctor.
Do not open it beforehand.
Keep out of children's reach.
Store below 25C, avoid direct sunlight.

KEEP OUT OF REACH OF CHILDREN

INDICATIONS AND USAGE

How to Use:
After washing face and evenly spreading the mask sheet on the face, keep the mask on for 15-20 minutes before peeling if off.
If there is residual essence on the face, gently tap on it so that they can be absorbed into the skin.

DOSAGE AND ADMINISTRATION

How to Use:
After washing face and evenly spreading the mask sheet on the face, keep the mask on for 15-20 minutes before peeling if off.
If there is residual essence on the face, gently tap on it so that they can be absorbed into the skin.